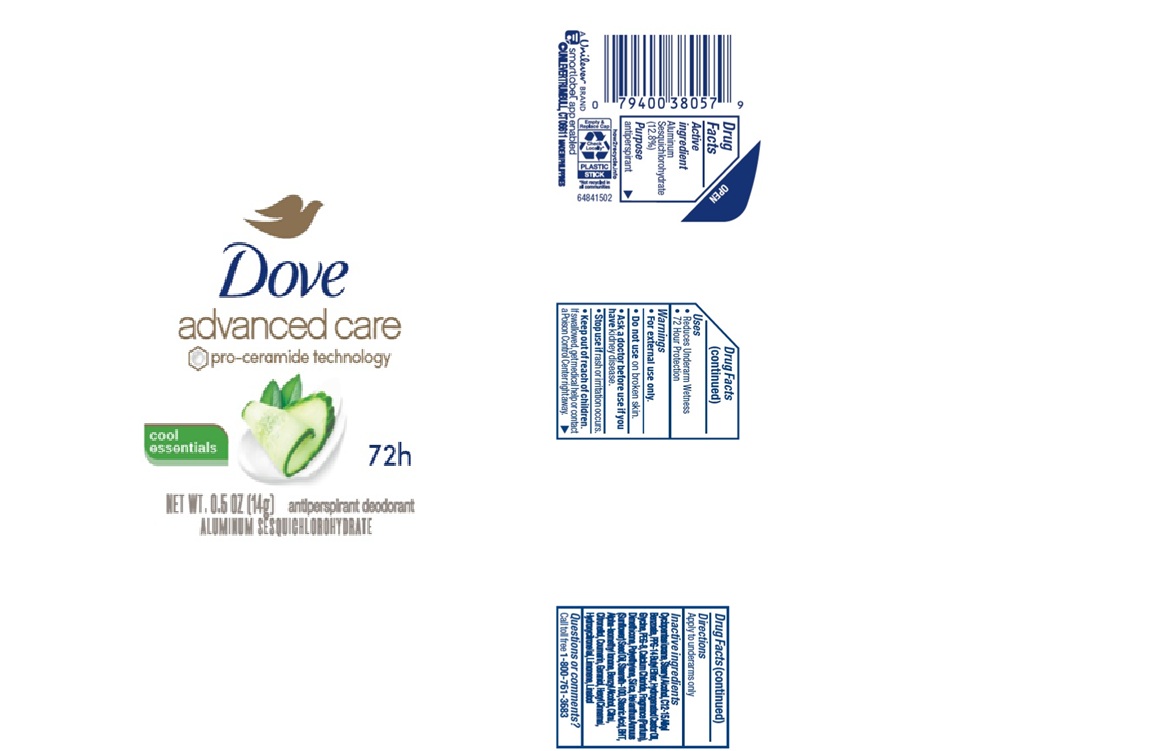 DRUG LABEL: Dove
NDC: 64942-2389 | Form: STICK
Manufacturer: Conopco Inc. d/b/a/ Unilever
Category: otc | Type: HUMAN OTC DRUG LABEL
Date: 20251010

ACTIVE INGREDIENTS: ALUMINUM SESQUICHLOROHYDRATE 12.8 g/100 g
INACTIVE INGREDIENTS: POLYETHYLENE; STEARETH-100; ALPHA-ISOMETHYL IONONE; COUMARIN; HEXYL CINNAMAL; C12-15 ALKYL BENZOATE; GERANIOL; BHT; PPG-14 BUTYL ETHER; PEG-8; CALCIUM CHLORIDE; SILICA; GLYCINE; DIMETHICONE; BENZYL ALCOHOL; CITRAL; LINALOOL; CYCLOPENTASILOXANE; STEARYL ALCOHOL; LIMONENE, (+)-; HYDROGENATED CASTOR OIL; STEARIC ACID; CITRONELLOL; HELIANTHUS ANNUUS (SUNFLOWER) SEED OIL; HYDROXYCITRONELLOL

DESCRIPTION

Dove Advanced Care Cool Essentials 72H Antiperspirant Deodorant

ACTIVE INGREDIENT

Aluminum Sesquichlorohydrate 12.8%

PURPOSE

antiperspirant
72 Hour Protection

INDICATIONS AND USAGE

reduces underarm wetness

WARNINGS

• For external use only.
• Do not use on broken skin.
• Ask a doctor before use if you have kidney disease.
• Stop use if rash or irritation occurs.

Keep out of reach of children.
If swallowed, get medical help or contact a Poison Control Center right away.

DOSAGE AND ADMINISTRATION

apply to underarms only

INACTIVE INGREDIENT

Cyclopentasiloxane, Stearyl Alcohol, C12-15 Alkyl Benzoate, PPG-14 Butyl Ether, Hydrogenated Castor Oil, Glycine, PEG-8, Calcium Chloride, Dimethicone, Polyethylene, Silica, Helianthus Annuus (Sunflower) Seed Oil, Steareth-100, Stearic Acid, BHT, Alpha-Isomethyl Ionone, Benzyl Alcohol, Citral, Citronellol, Coumarin, Geraniol, Hexyl Cinnamal, Hydroxycitronellol, Limonene, Linalool

QUESTIONS

Call toll-free 1-800-761-3683